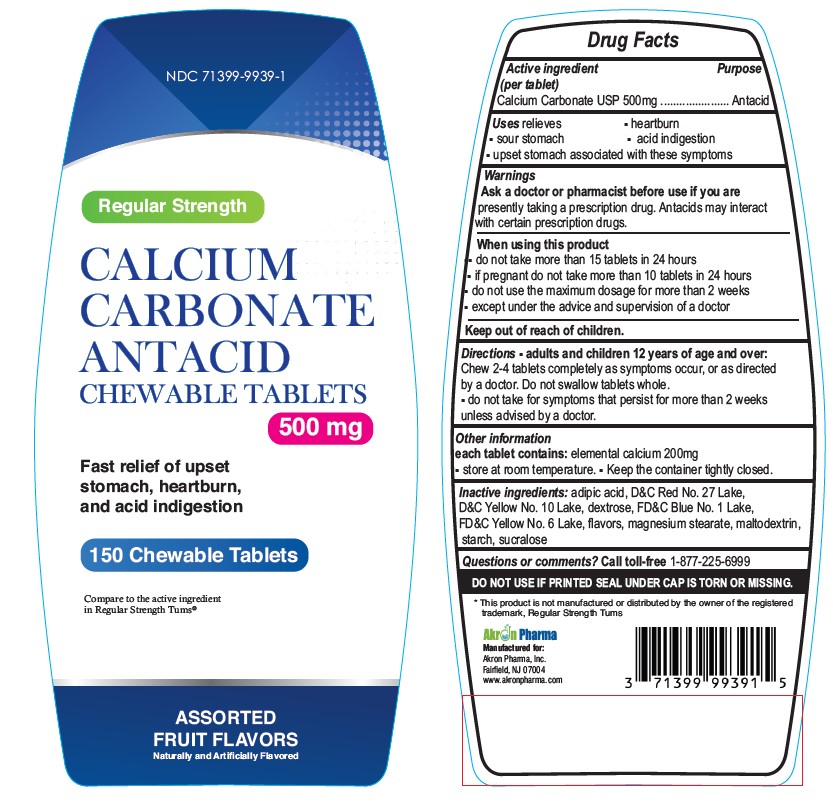 DRUG LABEL: Regular Strength
NDC: 71399-9939 | Form: TABLET, CHEWABLE
Manufacturer: AKRON PHARMA INC
Category: otc | Type: HUMAN OTC DRUG LABEL
Date: 20250923

ACTIVE INGREDIENTS: CALCIUM CARBONATE 500 mg/1 1
INACTIVE INGREDIENTS: D&C YELLOW NO. 10; DEXTROSE, UNSPECIFIED FORM; FD&C BLUE NO. 1; FD&C YELLOW NO. 6; MAGNESIUM STEARATE; MALTODEXTRIN; STARCH, CORN; SUCRALOSE; ADIPIC ACID; D&C RED NO. 27

Regular Strength Antacid Caclium Carbonate 150 Chewable Tablets

Active ingredient

Calcium Carbonate USP 500mg

Purpose

Antacid

Uses

relieves:

• heartburn

• sour stomach

• acid indigestion

• upset stomach associated with these symptoms

Warnings

Ask a doctor or pharmacist before use if you are presentlytaking a prescription drug. Antacids may interact with certain prescription drugs.

When using this product

- do not take more than 15 tablets in 24 hours
- If pregnant do not take more than 10 tablets in 24 hours
- do not use the maximum dosage for more than 2 weeks except under the advice and supervision of a doctor.

Keep out of Reach of Children

Directions

- Adults and children 12 years of age and over:chew 2-4 tablets as symptoms occur, or as directed by a doctor.
- Do not swallow tablets whole,
- Do not take for symptoms that persist for more than 2 weeks unless advised by a doctor.

Other Information

- Each tablet contains: elemental calcium 200 mg
- Store at room temperature. Keep the container tightly closed

Safety sealed: Do not use if printed seal under cap is torn or missing.

Inactive ingredients

adipic acid, D&C Red No.27 lake, D&C Yellow No.10 lake, dextrose, FD&C Blue No.1 lake, FD&C Yellow No.6 lake, flavors, magnesium stearate, maltodextrin, starch, sucralose.

Questions or comments? call toll-free 1-877-225-6999

Manufactured for:

Akron Pharma Inc.,

Fairfield, NJ-07004

www.akronpharma.com

*This product is not manufactured or distributed by GlaxoSmithKline LLC, owner of the registered trademark, Regular Strength Tums®.